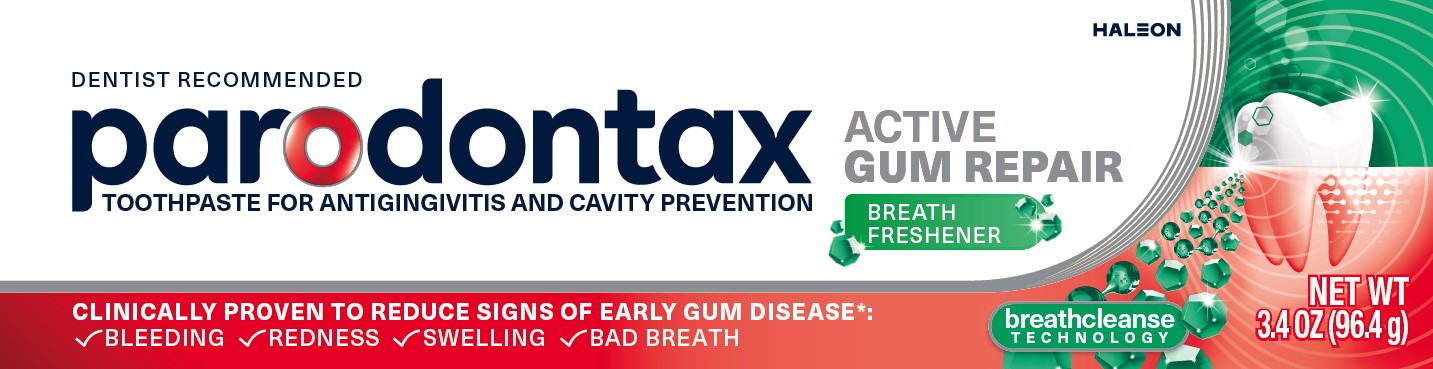 DRUG LABEL: parodontax
NDC: 0135-0737 | Form: PASTE
Manufacturer: Haleon US Holdings LLC
Category: otc | Type: HUMAN OTC DRUG LABEL
Date: 20251222

ACTIVE INGREDIENTS: STANNOUS FLUORIDE 1.10 mg/1 g
INACTIVE INGREDIENTS: GLYCERIN; POLYETHYLENE GLYCOL 400; HYDRATED SILICA; SODIUM TRIPOLYPHOSPHATE ANHYDROUS; SODIUM LAURYL SULFATE; TITANIUM DIOXIDE; POLYACRYLIC ACID (250000 MW); COCAMIDOPROPYL BETAINE; SACCHARIN SODIUM; ZINC CHLORIDE; CARRAGEENAN

Drug Facts

Active ingredient

Stannous fluoride 0.454% (0.15% w/v fluoride ion)

Purposes

Anticavity

Antigingivitis

Uses

- aids in the prevention of dental cavities.
- helps control bleeding gums.
- helps interfere with harmful effects of plaque associated with gingivitis.

Warnings

Stop use and ask a dentist if

- gingivitis, bleeding, or redness persists for more than 2 weeks.
- you have painful or swollen gums, pus from the gum line, loose teeth, or increasing spacing between the teeth. These may be signs or symptoms of periodontitis, a serious form of gum disease.

Keep out of reach of children under 6 years of age.

If more than used for brushing is accidentally swallowed, get medical help or contact a Poison Control Center right away.

Directions

- adults and children 2 years of age and older:
  - brush teeth thoroughly, preferably after each meal or at least twice a day, or as directed by a dentist or doctor. Minimize swallowing.
  - to minimize swallowing for children under 6 years of age, use a pea-sized amount and supervise brushing and rinsing until good habits are established.
- children under 2 years of age: Consult a dentist or doctor.

Other information

- products containing stannous fluoride may produce surface staining of the teeth. Adequate toothbrushing may prevent these stains which are not harmful or permanent and may be removed by your dentist.
- this product is specially formulated to help prevent staining.
- do not store above 25ºC (77ºF)

Inactive ingredients

glycerin, PEG-8, hydrated silica, pentasodium triphosphate, flavor, sodium lauryl sulfate, titanium dioxide, polyacrylic acid, cocamidopropyl betaine, sodium saccharin, zinc chloride, carrageenan

Questions or comments?

1-855-328-5202

Additional information

ALWAYS FOLLOW THE LABEL

parodontax ACTIVE GUM REPAIR
Bleeding, redness, swelling, and bad breath can be signs of gum disease.

parodontax Active Gum Repair Breath Freshener is a daily fluoride toothpaste that reduces signs of early gum disease and uses Breath Cleanse Technology to purify bad breath instead of just masking it. Specially formulated to kill plaque bacteria at the gumline to help keep the gum seal tight.

Its Breath Cleanse Technology utilizes zinc, an ingredient clinically proven to purify the gases that cause bad breath.

*vs. a regular toothpaste used by people who have gingivitis

Targets plaque bacteria

Fights early gum problems

Reduces bad breath

breathcleanse TECHNOLOGY

Principal Display Panel

DENTIST RECOMMENDED

parodontax

TOOTHPASTE FOR ANTIGINGIVITIS AND CAVITY PREVENTION

ACTIVE GUM REPAIR

BREATH FRESHENER

CLINICALLY PROVEN TO REDUCE SIGNS OF EARLY GUM DISEASE*:

✓ BLEEDING ✓ REDNESS ✓ SWELLING ✓BAD BREATH

breathcleanse

TECHNOLOGY

NET WT 3.4 OZ (96.4 g)